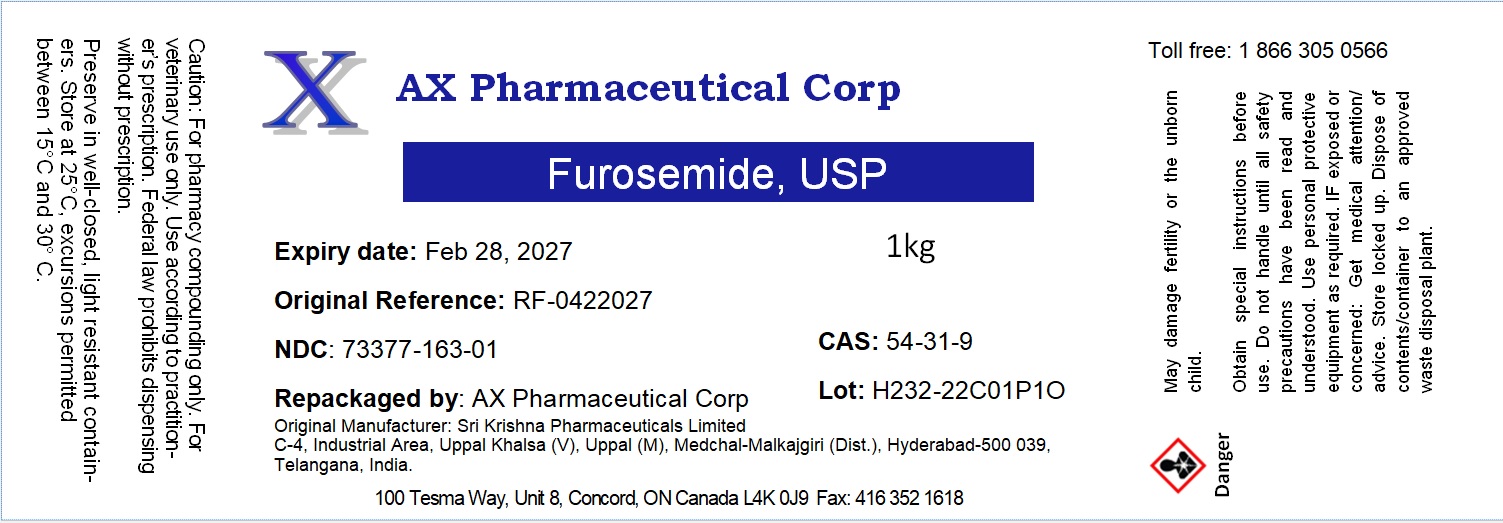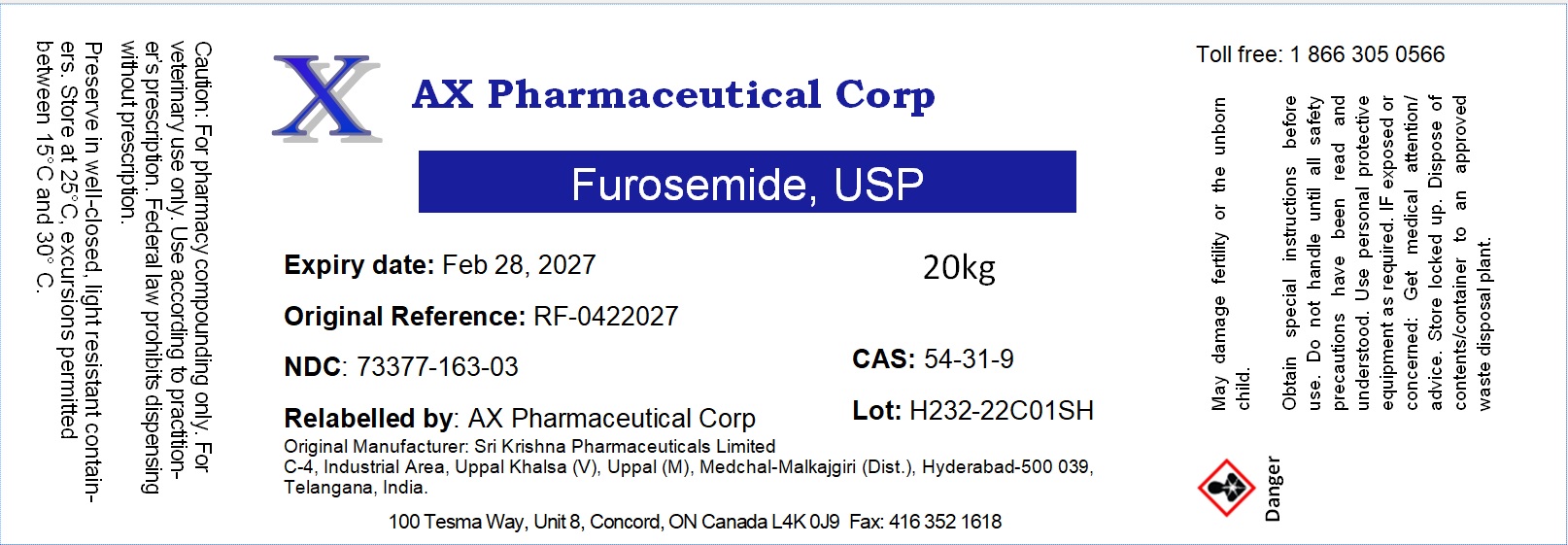 DRUG LABEL: Furosemide
NDC: 73377-163 | Form: POWDER
Manufacturer: AX Pharmaceutical Corp
Category: other | Type: BULK INGREDIENT - ANIMAL DRUG
Date: 20240314

ACTIVE INGREDIENTS: FUROSEMIDE 1 kg/1 kg

Furosemide